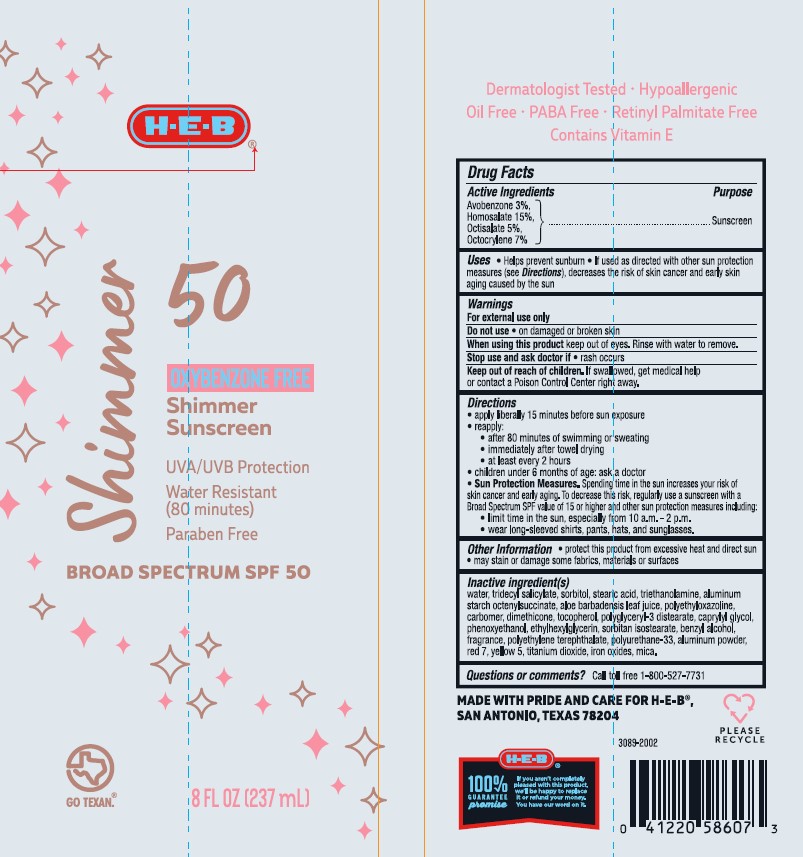 DRUG LABEL: HEB Shimmer Sunscreen SPF 50
NDC: 37808-041 | Form: LOTION
Manufacturer: H.E.B
Category: otc | Type: HUMAN OTC DRUG LABEL
Date: 20241015

ACTIVE INGREDIENTS: AVOBENZONE 30 mg/1 mL; HOMOSALATE 150 mg/1 mL; OCTISALATE 50 mg/1 mL; OCTOCRYLENE 70 mg/1 mL
INACTIVE INGREDIENTS: WATER; ALUMINUM STARCH OCTENYLSUCCINATE; BENZYL ALCOHOL; ALOE VERA LEAF; .ALPHA.-TOCOPHEROL, DL-; MICA; SORBITAN ISOSTEARATE; PHENOXYETHANOL; CAPRYLYL GLYCOL; TRIDECYL SALICYLATE; TITANIUM DIOXIDE; POLYETHYLOXAZOLINE (5000 MW); POLYGLYCERYL-3 DISTEARATE; POLYETHYLENE TEREPHTHALATE (INTRINSIC VISCOSITY 1.00-2.00); SORBITOL; ALUMINUM; D&C RED NO. 7; DIMETHICONE; TROLAMINE; ETHYLHEXYLGLYCERIN; FD&C YELLOW NO. 5; FERRIC OXIDE RED; CARBOMER INTERPOLYMER TYPE A (55000 CPS)

HEB Shimmer Sunscreen SPF 50 Lotion

Active Ingredients

Acobenzone 3.0%, Homosalate 15.0%, Octisalate 5.0%, Octocrylene 7.0%

Purpose

Sunscreen

Uses

- Helps prevent sunburn
- If used as directed with other sun protection measures (see Directions), decreases the risk of skin cancer and early skin aging caused by the sun

Warnings

For external use only

Do not use

• on damaged or broken skin

When using this product

keep out of eyes. Rinse with water to remove.

Stop use and ask doctor if

• rash occurs

Keep out of reach of children.

If swallowed, get medical help or contact a Poison Control Center right away.

Directions

- apply liberally 15 minutes before sun exposure
- reapply:

• after 80 minutes of swimming or sweating

• immediately after towel drying

• at least every 2 hours

- children under 6 months of age: Ask a doctor
- Sun Protection Measures. Spending time in the sun increases your risk of skin cancer and early aging. To decrease this risk, regularly use a sunscreen with a Broad Spectrum value of 15 or higher and other sun protection measures including:

• limit time in the sun, especially from 10am-2pm

• wear long-sleeved shirts, pants, hats, and sunglasses.

Other Information

- protect the product in this container from excessive heat and direct sun
- may stain or damage some fabrics, materials or surfaces

Inactive Ingredient(s)

water, tridecyl salicylate, sorbitol, stearic acid, triethanolamine, aluminum starch octenylsuccinate, aloe barbadensis leaf juice, polyethyloxazoline, carbomer, dimethicone, tocopherol, polyglyceryl-3 distearate, caprylyl glycol, phenoxyethanol, ethylhexylglycerin, sorbitan isostearate, benzyl alcohol, fragrance, polyethylene terephthalate, polyurethane-33, aluminum powder, red 7, yellow 5, titanium dioxide, iron oxides, mica